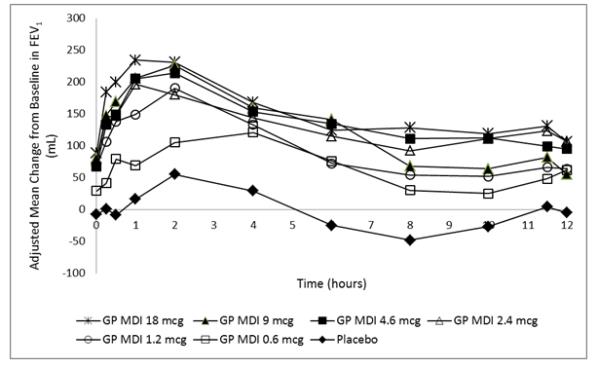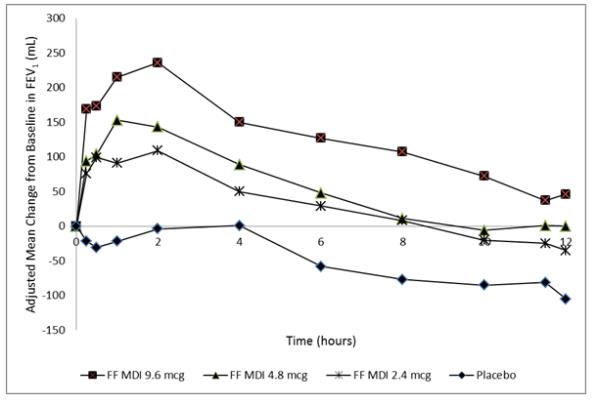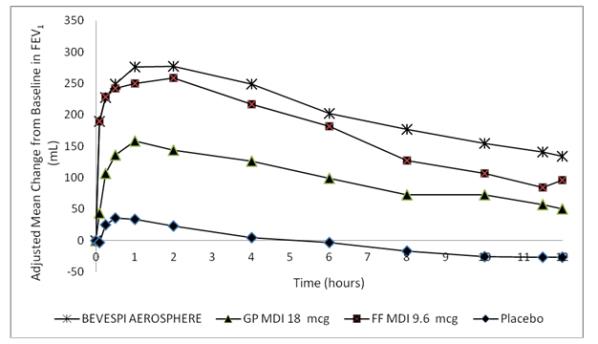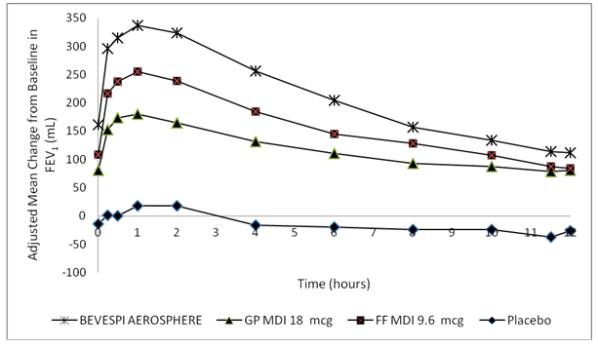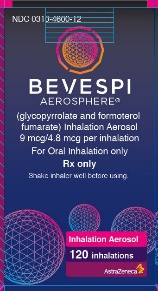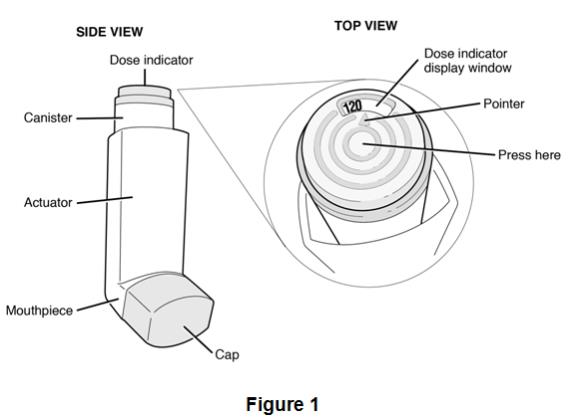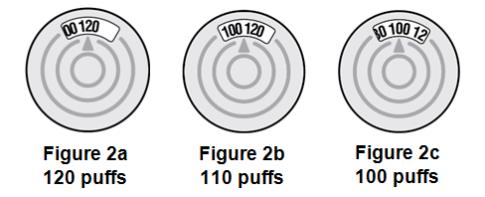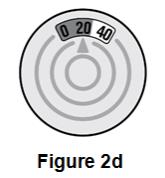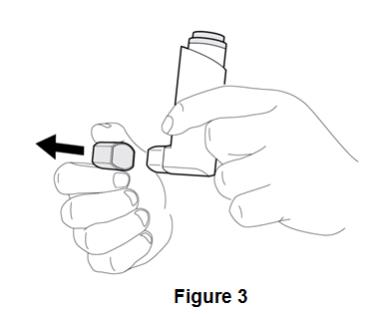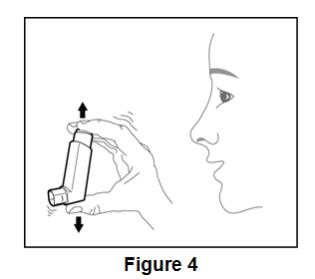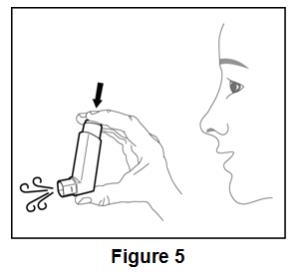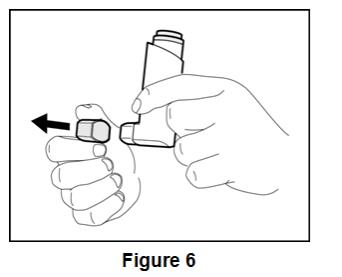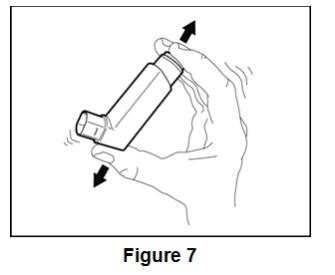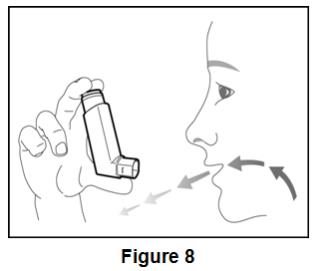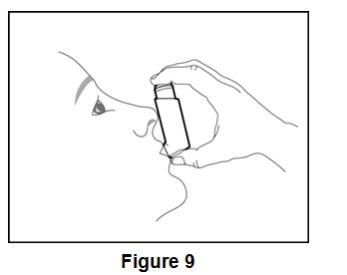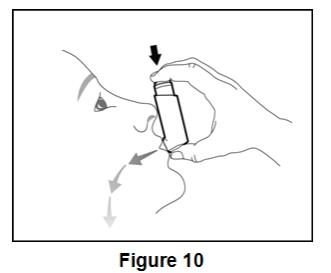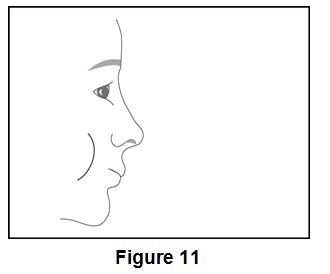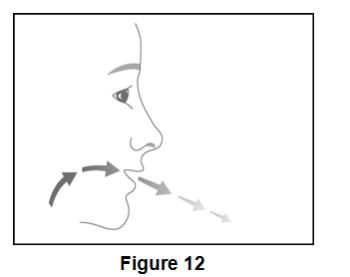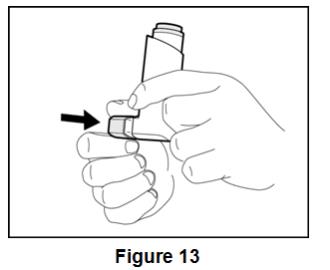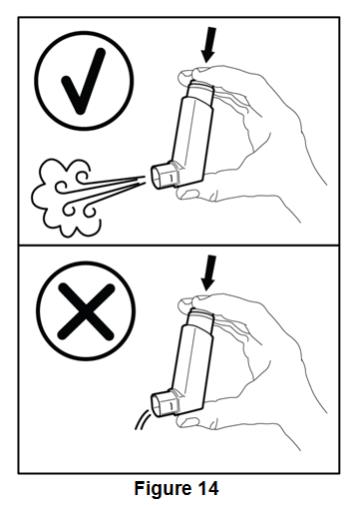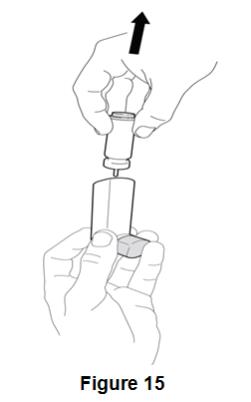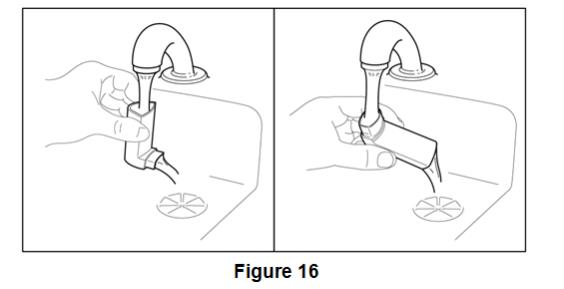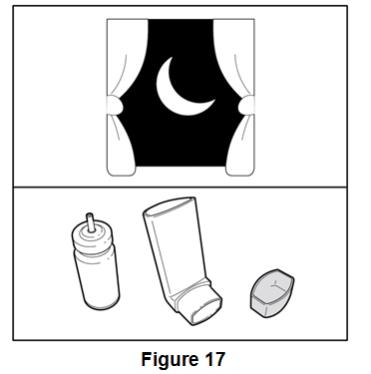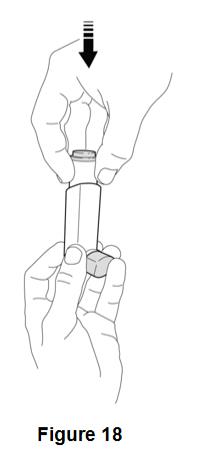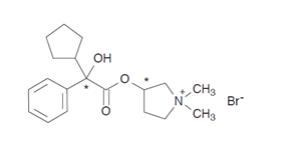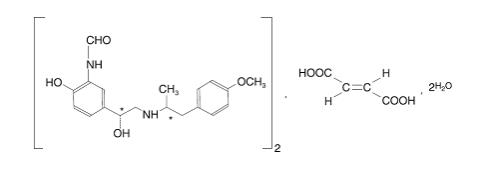 DRUG LABEL: BEVESPI AEROSPHERE
NDC: 0310-4600 | Form: AEROSOL, METERED
Manufacturer: AstraZeneca Pharmaceuticals LP
Category: prescription | Type: HUMAN PRESCRIPTION DRUG LABEL
Date: 20230324

ACTIVE INGREDIENTS: GLYCOPYRROLATE 9 ug/1 1; FORMOTEROL FUMARATE 4.8 ug/1 1
INACTIVE INGREDIENTS: 1,2-DISTEAROYL-SN-GLYCERO-3-PHOSPHOCHOLINE; CALCIUM CHLORIDE; NORFLURANE

HIGHLIGHTS OF PRESCRIBING INFORMATION

These highlights do not include all the information needed to use BEVESPI AEROSPHERE safely and effectively. See full prescribing information for BEVESPI AEROSPHERE.
BEVESPI AEROSPHERE® (glycopyrrolate and formoterol fumarate) inhalation aerosol, for oral inhalation use
Initial U.S. Approval: 2016

1 INDICATIONS AND USAGE

BEVESPI AEROSPHERE is a combination of glycopyrrolate, an anticholinergic, and formoterol fumarate, a long-acting beta2-adrenergic agonist (LABA) indicated for the maintenance treatment of patients with chronic obstructive pulmonary disease (COPD). (1)

Limitations of Use: Not indicated for the relief of acute bronchospasm or for the treatment of asthma. (1, 5.1, 5.2)

2 DOSAGE AND ADMINISTRATION

- For oral inhalation only.
- Maintenance treatment of COPD: 2 inhalations of BEVESPI AEROSPHERE twice daily by oral inhalation. (2)

3 DOSAGE FORMS AND STRENGTHS

- Inhalation aerosol: pressurized metered dose inhaler containing a combination of glycopyrrolate (9 mcg) and formoterol fumarate (4.8 mcg) per inhalation.

4 CONTRAINDICATIONS

- Use of a LABA, including formoterol fumarate, one of the active ingredients in BEVESPI AEROSPHERE, without an inhaled corticosteroid is contraindicated in patients with asthma. (4)
- Hypersensitivity to glycopyrrolate, formoterol fumarate, or to any component of this product. (4, 5.5)

5 WARNINGS AND PRECAUTIONS

- LABA as monotherapy (without an inhaled corticosteroid) for asthma increases the risk of serious asthma-related events. (5.1)
- Do not initiate in acutely deteriorating COPD or to treat acute symptoms. (5.2)
- Do not use in combination with an additional therapy containing a LABA because of risk of overdose. (5.3, 7.1)
- If paradoxical bronchospasm occurs, discontinue BEVESPI AEROSPHERE and institute alternative therapy. (5.4)
- Use with caution in patients with cardiovascular disorders. (5.6)
- Worsening of narrow-angle glaucoma may occur. Use with caution in patients with narrow-angle glaucoma and instruct patients to contact a physician immediately if symptoms occur. (5.7)
- Worsening urinary retention may occur. Use with caution in patients with prostatic hyperplasia or bladder-neck obstruction and instruct patients to contact a physician immediately if symptoms occur. (5.8)
- Use with caution in patients with convulsive disorders, thyrotoxicosis, diabetes mellitus, and ketoacidosis. (5.9)
- Be alert to hypokalemia and hyperglycemia. (5.10)

6 ADVERSE REACTIONS

Most common adverse reactions (incidence ≥2% and more common than with placebo) include: urinary tract infection and cough. (6.1)

To report SUSPECTED ADVERSE REACTIONS, contact AstraZeneca at 1-800-236-9933 or FDA at 1-800-FDA-1088 or www.fda.gov/medwatch.

7 DRUG INTERACTIONS

- Other adrenergic drugs may potentiate effect: Use with caution (5.3, 7.1)
- Xanthine derivatives, steroids, diuretics or non-potassium sparing diuretics may potentiate hypokalemia or ECG changes. Use with caution. (7.2, 7.3)
- Diuretics: Use with caution. Electrocardiographic changes and/or hypokalemia associated with non-potassium sparing diuretics may worsen with concomitant beta2-agonists. (7.3)
- Monoamine oxidase inhibitors and tricyclic antidepressants: Use with extreme caution. May potentiate effect of formoterol fumarate on cardiovascular system. (7.4)
- Beta-blockers: Use with caution and only when medically necessary. (7.5)
- Anticholinergics: May interact additively with concomitantly used anticholinergic medications. Avoid administrations of BEVESPI AEROSPHERE with other anticholinergic-containing drugs. (7.6)

8 USE IN SPECIFIC POPULATIONS

- In patients with severe renal impairment use should be considered only if the potential benefit of the treatment outweighs the risk. (8.7)

FULL PRESCRIBING INFORMATION

1 INDICATIONS AND USAGE

BEVESPI AEROSPHERE is indicated for the maintenance treatment of patients with chronic obstructive pulmonary disease (COPD).

Limitations of Use:

BEVESPI AEROSPHERE is not indicated for the relief of acute bronchospasm or for the treatment of asthma [see Warnings and Precautions (5.1, 5.2)].

2 DOSAGE AND ADMINISTRATION

2.1 Recommended Dosage and Administration

The recommended dosage of BEVESPI AEROSPHERE is glycopyrrolate 18 mcg and formoterol fumarate 9.6 mcg (administered as two inhalations of BEVESPI AEROSPHERE [glycopyrrolate/formoterol fumarate 9 mcg/4.8 mcg]) twice daily in the morning and in the evening by oral inhalation. Do not take more than two inhalations twice daily.

2.2 Preparation

Prime BEVESPI AEROSPHERE before using for the first time. Priming BEVESPI AEROSPHERE is essential to ensure appropriate drug content in each actuation. To prime BEVESPI AEROSPHERE, release 4 sprays into the air away from the face, shaking well before each spray. BEVESPI AEROSPHERE must be re-primed when the inhaler has not been used for more than 7 days. To re-prime BEVESPI AEROSPHERE, release 2 sprays into the air away from the face, shaking well before each spray.

2.3 Dose Counter

The canister has an attached dose indicator, which indicates how many inhalations remain. The dose indicator display will move after every tenth actuation. When nearing the end of the usable inhalations, the color behind the number in the dose indicator display window changes to red. BEVESPI AEROSPHERE should be discarded when the dose indicator display window shows zero.

3 DOSAGE FORMS AND STRENGTHS

Inhalation aerosol: pressurized metered dose inhaler that delivers 9 mcg of glycopyrrolate and 4.8 mcg of formoterol fumarate per inhalation.

4 CONTRAINDICATIONS

BEVESPI AEROSPHERE is contraindicated in:

- use of a long-acting beta2-adrenergic agonist (LABA), including formoterol fumarate, one of the active ingredients in BEVESPI AEROSPHERE, without an inhaled corticosteroid, in patients with asthma [see Warnings and Precautions (5.1)]. BEVESPI AEROSPHERE is not indicated for the treatment of asthma.
- patients with hypersensitivity to glycopyrrolate, formoterol fumarate, or to any component of the product [see Warnings and Precautions (5.5)].

5 WARNINGS AND PRECAUTIONS

5.1 Serious Asthma-Related Events – Hospitalizations, Intubations, Death

- The safety and efficacy of BEVESPI AEROSPHERE in patients with asthma have not been established. BEVESPI AEROSPHERE is not indicated for the treatment of asthma [see Contraindications (4)].
- Use of LABA as monotherapy [without inhaled corticosteroids (ICS)] for asthma is associated with an increased risk of asthma-related death. Available data from controlled clinical trials also suggest that use of LABA as monotherapy increases the risk of asthma-related hospitalization in pediatric and adolescent patients. These findings are considered a class effect of LABA monotherapy. When LABA are used in fixed-dose combination with ICS, data from large clinical trials do not show a significant increase in the risk of serious asthma-related events (hospitalizations, intubations, death) compared with ICS alone.
- A 28-week, placebo-controlled US trial comparing the safety of another LABA (salmeterol) with placebo, each added to usual asthma therapy, showed an increase in asthma-related deaths in subjects receiving salmeterol (13/13,176 in subjects treated with salmeterol vs. 3/13,179 in subjects treated with placebo; RR 4.37, 95% CI: 1.25, 15.34). The increased risk of asthma-related death is considered a class effect of LABAs, including formoterol fumarate, one of the active ingredients in BEVESPI AEROSPHERE.
- No trial adequate to determine whether the rate of asthma-related deaths is increased in patients treated with BEVESPI AEROSPHERE has been conducted.
- Available data do not suggest an increased risk of death with use of LABA in patients with COPD.

5.2 Deterioration of Disease and Acute Episodes

BEVESPI AEROSPHERE should not be initiated in patients with acutely deteriorating COPD, which may be a life-threatening condition. BEVESPI AEROSPHERE has not been studied in patients with acutely deteriorating COPD. The use of BEVESPI AEROSPHERE in this setting is inappropriate.

BEVESPI AEROSPHERE should not be used for the relief of acute symptoms, i.e., as rescue therapy for the treatment of acute episodes of bronchospasm. BEVESPI AEROSPHERE has not been studied in the relief of acute symptoms and extra doses should not be used for that purpose. Acute symptoms should be treated with an inhaled short-acting beta2-agonist.

When beginning BEVESPI AEROSPHERE, patients who have been taking inhaled, short-acting beta2-agonists on a regular basis (e.g., four times a day) should be instructed to discontinue the regular use of these medicines and use them only for symptomatic relief of acute respiratory symptoms. When prescribing BEVESPI AEROSPHERE, the healthcare provider should also prescribe an inhaled, short acting beta2-agonist and instruct the patient on how it should be used. Increasing inhaled beta2-agonist use is a signal of deteriorating disease for which prompt medical attention is indicated.

COPD may deteriorate acutely over a period of hours or chronically over several days or longer. If BEVESPI AEROSPHERE no longer controls the symptoms of bronchoconstriction, or the patient’s inhaled, short-acting beta2-agonist becomes less effective, or the patient needs more inhalations of short-acting beta2-agonist than usual, these may be markers of deterioration of disease. In this setting, a re-evaluation of the patient and the COPD treatment regimen should be undertaken at once. Increasing the daily dosage of BEVESPI AEROSPHERE beyond the recommended dose is not appropriate in this situation.

5.3 Avoid Excessive Use of BEVESPI and Avoid Use with Other Long-Acting Beta2-Agonists

As with other inhaled medicines containing beta2-agonists, BEVESPI AEROSPHERE should not be used more often than recommended, at higher doses than recommended, or in conjunction with other medications containing LABAs, as an overdose may result. Clinically significant cardiovascular effects and fatalities have been reported in association with excessive use of inhaled sympathomimetic medicines. Patients using BEVESPI AEROSPHERE should not use another medicine containing a LABA for any reason [see Drug Interactions (7.1)].

5.4 Paradoxical Bronchospasm

As with other inhaled medicines, BEVESPI AEROSPHERE can produce paradoxical bronchospasm, which may be life threatening. If paradoxical bronchospasm occurs following dosing with BEVESPI AEROSPHERE, it should be treated immediately with an inhaled, short-acting bronchodilator, BEVESPI AEROSPHERE should be discontinued immediately, and alternative therapy should be instituted.

5.5 Hypersensitivity Reactions including Anaphylaxis

Immediate hypersensitivity reactions have been reported after administration of glycopyrrolate or formoterol fumarate, the components of BEVESPI AEROSPHERE. If signs suggesting allergic reactions occur, in particular, angioedema (including difficulties in breathing or swallowing, swelling of tongue, lips, and face), urticaria, or skin rash, BEVESPI AEROSPHERE should be stopped at once and alternative treatment should be considered.

5.6 Cardiovascular Effects

Formoterol fumarate, like other beta2-agonists, can produce a clinically significant cardiovascular effect in some patients as measured by increases in pulse rate, systolic or diastolic blood pressure, or symptoms [see Clinical Pharmacology (12.2)]. If such effects occur, BEVESPI AEROSPHERE may need to be discontinued. In addition, beta-agonists have been reported to produce electrocardiographic changes, such as flattening of the T wave, prolongation of the QTc interval, and ST segment depression, although the clinical significance of these findings is unknown.

Therefore, BEVESPI AEROSPHERE should be used with caution in patients with cardiovascular disorders, especially coronary insufficiency, cardiac arrhythmias, and hypertension.

5.7 Worsening of Narrow-Angle Glaucoma

BEVESPI AEROSPHERE should be used with caution in patients with narrow-angle glaucoma. Prescribers and patients should be alert for signs and symptoms of acute narrow-angle glaucoma (e.g., eye pain or discomfort, blurred vision, visual halos, or colored images in association with red eyes from conjunctival congestion and corneal edema). Instruct patients to consult a physician immediately should any of these signs or symptoms develop.

5.8 Worsening of Urinary Retention

BEVESPI AEROSPHERE should be used with caution in patients with urinary retention. Prescribers and patients should be alert for signs and symptoms of urinary retention (e.g., difficulty passing urine, painful urination), especially in patients with prostatic hyperplasia or bladder-neck obstruction. Instruct patients to consult a physician immediately should any of these signs or symptoms develop.

5.9 Coexisting Conditions

BEVESPI AEROSPHERE, like all medications containing sympathomimetic amines, should be used with caution in patients with convulsive disorders or thyrotoxicosis and in those who are unusually responsive to sympathomimetic amines. Doses of the related beta2-agonist albuterol, when administered intravenously, have been reported to aggravate pre-existing diabetes mellitus and ketoacidosis.

5.10 Hypokalemia and Hyperglycemia

Beta2-agonist medications may produce significant hypokalemia in some patients, possibly through intracellular shunting, which has the potential to produce adverse cardiovascular effects [see Clinical Pharmacology (12.2)]. The decrease in serum potassium is usually transient, not requiring supplementation. Beta2-agonist medicines may produce transient hyperglycemia in some patients. In two clinical trials of 24-weeks and a 28-week safety extension study evaluating BEVESPI AEROSPHERE in subjects with COPD, there was no evidence of a treatment effect on serum glucose or potassium.

6 ADVERSE REACTIONS

The following adverse reactions are described in greater detail elsewhere in the labeling:

- Paradoxical bronchospasm [see Warnings and Precautions (5.4)]
- Hypersensitivity reactions including Anaphylaxis [see Contraindications (4), Warnings and Precautions (5.5)]
- Cardiovascular effects [see Warnings and Precautions (5.6)]
- Worsening of narrow-angle glaucoma [see Warnings and Precautions (5.7)]
- Worsening of urinary retention [see Warnings and Precautions (5.8)]

6.1 Clinical Trials Experience

Because clinical trials are conducted under widely varying conditions, adverse reaction rates observed in the clinical trials of a drug cannot be directly compared with rates in the clinical trials of another drug and may not reflect the rates observed in practice.

The clinical program for BEVESPI AEROSPHERE included 4,911 subjects with COPD in two 24-week lung function trials, one long-term safety extension study of 28 weeks, and 10 other trials of shorter duration. A total of 1,302 subjects have received at least 1 dose of BEVESPI AEROSPHERE. The safety data described below are based on the two 24-week trials and the one 28-week long-term safety extension trial. Adverse reactions observed in the other trials were similar to those observed in these confirmatory trials.

24-Week Trials

The incidence of adverse reactions with BEVESPI AEROSPHERE in Table 1 is based on reports in two 24-week, placebo-controlled trials (Trials 1 and 2; n=2,100 and n=1,610, respectively). Of the 3,710 subjects, 56% were male and 91% were Caucasian. They had a mean age of 63 years and an average smoking history of 51 pack-years, with 54% identified as current smokers. At screening, the mean post-bronchodilator percent predicted forced expiratory volume in 1 second (FEV1) was 51% (range: 19% to 82%) and the mean percent reversibility was 20% (range: -32% to 135%).

Subjects received one of the following treatments: BEVESPI AEROSPHERE, glycopyrrolate 18 mcg, formoterol fumarate 9.6 mcg, or placebo twice daily or active control.

Table 1 - Adverse Reactions with BEVESPI AEROSPHERE ≥2% Incidence and More
Common than with Placebo in Subjects with Chronic Obstructive Pulmonary Disease

Adverse Reaction | BEVESPI AEROSPHERE (n=1036) % | Glycopyrrolate 18 mcg BID (n=890) % | Formoterol Fumarate 9.6 mcg BID (n=890) % | Placebo (n=443) %
Respiratory, thoracic, and mediastinal disorders
Cough | 4.0 | 3.0 | 2.7 | 2.7
Infections and infestation
Urinary tract infection | 2.6 | 1.8 | 1.5 | 2.3

Other adverse reactions defined as events with an incidence of >1% but less than 2% with BEVESPI AEROSPHERE but more common than with placebo included the following: arthralgia, chest pain, tooth abscess, muscle spasms, headache, oropharyngeal pain, vomiting, pain in extremity, dizziness, anxiety, dry mouth, fall, influenza, fatigue, acute sinusitis, and contusion.

Long-Term Safety Extension Trial

In a 28-week long-term safety extension trial, 893 subjects who successfully completed Trial 1 or Trial 2 were treated for up to an additional 28 weeks for a total treatment period of up to 52 weeks with BEVESPI AEROSPHERE, glycopyrrolate 18 mcg, formoterol fumarate 9.6 mcg administered twice daily or active control. Because the subjects continued from Trial 1 or Trial 2 into the safety extension trial, the demographic and baseline characteristics of the long-term safety extension trial were similar to those of the placebo-controlled efficacy trials described above. The adverse reactions reported in the long-term safety trial were consistent with those observed in the 24-week placebo-controlled trials.

Additional Adverse Reactions: Other adverse reactions that have been associated with the component formoterol fumarate include: hypersensitivity reactions, hyperglycemia, sleep disturbance, agitation, restlessness, tremor, nausea, tachycardia, palpitations, cardiac arrhythmias (atrial fibrillation, supraventricular tachycardia, and extrasystoles).

6.2 Postmarketing Experience

The following adverse reactions have been identified during post approval use of BEVESPI AEROSPHERE. Because these reactions are reported voluntarily from a population of uncertain size, it is not always possible to reliably estimate their frequency or establish a causal relationship to drug exposure.

In postmarketing experience with BEVESPI AEROSPHERE, hypersensitivity and urinary retention have been reported.

7 DRUG INTERACTIONS

No formal drug interaction studies have been performed with BEVESPI AEROSPHERE.

7.1 Adrenergic Drugs

If additional adrenergic drugs are to be administered by any route, they should be used with caution because the sympathetic effects of formoterol, a component of BEVESPI AEROSPHERE, may be potentiated [see Warnings and Precautions (5.3)].

7.2 Xanthine Derivatives, Steroids, or Diuretics

Concomitant treatment with xanthine derivatives, steroids, or diuretics may potentiate any hypokalemic effect of beta2 adrenergic agonists such as formoterol, a component of BEVESPI AEROSPHERE.

7.3 Non-Potassium Sparing Diuretics

The ECG changes and/or hypokalemia that may result from the administration of non-potassium-sparing diuretics (such as loop or thiazide diuretics) can be acutely worsened by beta2-agonists, especially when the recommended dose of the beta2-agonist is exceeded. Approximately 17% of subjects were taking non-potassium sparing diuretics during the two 24-week placebo-controlled trials in subjects with COPD. The incidence of adverse events in subjects taking non-potassium-sparing diuretics was similar between BEVESPI AEROSPHERE and placebo treatment groups. In addition, there was no evidence of a treatment effect on serum potassium with BEVESPI AEROSPHERE compared to placebo in subjects taking non-potassium sparing diuretics during the two 24-week trials. However, caution is advised in the coadministration of BEVESPI AEROSPHERE with non-potassium-sparing diuretics.

7.4 Monoamine Oxidase Inhibitors, Tricyclic Antidepressants, QTc Prolonging Drugs

BEVESPI AEROSPHERE, as with other beta2-agonists, should be administered with extreme caution to patients being treated with monoamine oxidase inhibitors or tricyclic antidepressants or other drugs known to prolong the QTc interval because the action of adrenergic agonists on the cardiovascular system may be potentiated by these agents. Drugs that are known to prolong the QTc interval may be associated with an increased risk of ventricular arrhythmias.

7.5 Beta-Blockers

Beta-adrenergic receptor antagonists (beta-blockers) and BEVESPI AEROSPHERE may interfere with the effect of each other when administered concurrently. Beta-blockers not only block the therapeutic effects of beta2-agonists, but may produce severe bronchospasm in COPD patients. Therefore, patients with COPD should not normally be treated with beta-blockers. However, under certain circumstances, e.g., as prophylaxis after myocardial infarction, there may be no acceptable alternatives to the use of beta-blockers in patients with COPD. In this setting, cardioselective beta-blockers could be considered, although they should be administered with caution.

7.6 Anticholinergics

There is a potential for an additive interaction with concomitantly used anticholinergic medications. Therefore, avoid coadministration of BEVESPI AEROSPHERE with other anticholinergic-containing drugs as this may lead to an increase in anticholinergic adverse effects [see Warnings and Precautions (5.7, 5.8) and Adverse Reactions (6)].

8 USE IN SPECIFIC POPULATIONS

8.1 Pregnancy

Risk Summary

There are no adequate and well-controlled trials of BEVESPI AEROSPHERE or its individual components, glycopyrrolate and formoterol fumarate, in pregnant women to inform a drug-associated risk.

In animal reproduction studies, glycopyrrolate alone, administered by the subcutaneous route in rats and rabbits, did not cause structural abnormalities or affect fetal survival at exposures approximately 2700 and 5400 times from the maximum recommended human daily inhalation dose (MRHDID), respectively. Glycopyrrolate had no effects on the physical, functional, and behavioral development of rat pups with exposures up to 2700 times the MRHDID.

Formoterol fumarate alone, administered by the oral route in rats and rabbits, caused structural abnormalities at 1500 and 61,000 times the MRHDID, respectively. Formoterol fumarate was also embryocidal, increased pup loss at birth and during lactation, and decreased pup weight in rats at 110 times the MRHDID. These adverse effects generally occurred at large multiples of the MRHDID when formoterol fumarate was administered by the oral route to achieve high systemic exposures. No structural abnormalities, embryocidal, or developmental effects were seen in rats that received inhalation doses up to 350 times the MRHDID.

The estimated background risk of major birth defects and miscarriage for the indicated population is unknown. In the U.S. general population, the estimated background risk of major birth defects and miscarriage in clinically recognized pregnancies is 2-4% and 15-20%, respectively.

Clinical Considerations

Labor or Delivery: There are no well-controlled human trials that have investigated the effects of BEVESPI AEROSPHERE on preterm labor or labor at term. Because beta2-agonists may potentially interfere with uterine contractility, BEVESPI AEROSPHERE should be used during labor only if the potential benefit justifies the potential risk.

Data

Animal Data

Glycopyrrolate

In an embryo-fetal development study in pregnant rats dosed during the period of organogenesis from gestation days 6 to 17, glycopyrrolate produced no structural abnormalities or effects on fetal survival; however, slight reductions of fetal body weight in the presence of maternal toxicity at the highest tested dose that was 2700 times the MRHDID (on a mcg/m^2 basis at a maternal subcutaneous dose of 10,000 mcg/kg/day). Fetal body weights were unaffected with doses up to 270 times the MRHDID (on a mcg/m^2 basis with maternal subcutaneous doses up to 1000 mcg/kg/day). Maternal toxicity was observed with doses 270 times the MRHDID and higher (on a mcg/m^2 basis with maternal subcutaneous doses of 1000 mcg/kg/day and higher).

In an embryo-fetal development study in pregnant rabbits dosed during the period of organogenesis from gestation days 6 to 18, glycopyrrolate produced no structural abnormalities or effects on fetal survival; however, slight reductions of fetal body weight in the presence of maternal toxicity at the highest tested dose that was 5400 times the MRHDID (on a mcg/m^2 basis at a maternal subcutaneous dose of 10,000 mcg/kg/day). Fetal body weights were unaffected with doses up to 540 times the MRHDID (on a mcg/m^2 basis with maternal subcutaneous doses up to 1000 mcg/kg/day). Maternal toxicity was observed with doses 540 times the MRHDID and higher (on a mcg/m^2 basis with maternal subcutaneous doses of 1000 mcg/kg/day and higher).

In a pre- and post-natal development study, pregnant female rats received glycopyrrolate at doses of 100, 1000, and 10,000 mcg/kg/day from gestation day 6 through the lactation period. Pup body weight gain was slightly reduced from birth through the lactation period at a dose 2700 times the MRHDID (on a mcg/m^2 basis with a maternal subcutaneous dose of 10,000 mcg/kg/day); however, pup body weight gain was unaffected after weaning There were no treatment-related effects on the physical, functional, and behavioral development of pups with doses up to 2700 times the MRHDID (on a mcg/m^2 basis with maternal subcutaneous doses up to 10,000 mcg/kg/day). Maternal toxicity was observed from gestation days 6 to 18 with doses 270 times the MRHDID and higher (on a mcg/m^2 basis with maternal subcutaneous doses of 1000 mcg/kg/day and higher).

Formoterol Fumarate

In a fertility and reproduction study, male rats were orally dosed for at least 9 weeks and females for 2 weeks prior to pairing and throughout the mating period. Females were either dosed up to gestation day 19 or up until weaning of their offspring. Males were dosed up to 25 weeks. Umbilical hernia was observed in rat fetuses at oral doses 1500 times the MRHDID (on a mcg/m^2 basis at maternal oral doses of 3000 mcg/kg/day and higher). Brachygnathia was observed in rat fetuses at a dose 8000 times the MRHDID (on a mcg/m^2 basis at a maternal oral dose of 15,000 mcg/kg/day). Pregnancy was prolonged at a dose 8000 times the MRHDID (on a mcg/m^2 basis at a maternal oral dose of 15,000 mcg/kg/day). Fetal and pup deaths occurred at doses approximately 1500 times the MRHDID and higher (on a mcg/m^2 basis at oral doses of 3000 mcg/kg/day and higher) during gestation.

In an embryo-fetal development study in pregnant rats dosed during the period of organogenesis, no structural abnormalities, embryocidal effects, or developmental effects were seen at doses up to 350 times the MRHDID (on a mcg/m^2 basis with maternal inhalation doses up to 690 mcg/kg/day).

In an embryo-fetal development study in pregnant rabbits dosed during the period of organogenesis from gestation days 6 to 18, subcapsular cysts on the liver were observed in the fetuses at a dose 61,000 times the MRHDID (on a mcg/m^2 basis with a maternal oral dose of 60,000 mcg/kg/day). No teratogenic effects were observed at doses up to 3500 times the MRHDID (on a mcg/m^2 basis at maternal oral doses up to 3500 mcg/kg/day).

In a pre- and post-natal development study, pregnant female rats received formoterol at oral doses of 0, 210, 840, and 3400 mcg/kg/day from gestation day 6 (completion of implantation) through the lactation period. Pup survival was decreased from birth to postpartum day 26 at doses 110 times the MRHDID and higher (on a mcg/m^2 basis at maternal oral doses of 210 mcg/kg/day and higher), although there was no evidence of a dose-response relationship. There were no treatment-related effects on the physical, functional, and behavioral development of rat pups.

8.2 Lactation

Risk Summary

There are no available data on the effects of BEVESPI AEROSPHERE, glycopyrrolate, or formoterol fumarate on the breastfed child or on milk production. There are no available data on the presence of glycopyrrolate or formoterol fumarate in human milk. Formoterol fumarate and glycopyrrolate have been detected in the plasma of undosed rat pups suckling from exposed dams [see Data]. The developmental and health benefits of breastfeeding should be considered along with the mother's clinical need for BEVESPI AEROSPHERE and any potential adverse effects on the breast-fed child from BEVESPI AEROSPHERE or from the underlying maternal condition.

Animal Data

In the reproductive/developmental toxicity study in rats, plasma levels of glycopyrrolate were measured in pups on post-natal day 4. The maximum concentration in the pups was 6% of the maternal dose of 10 mg/kg/day (pup plasma concentration of 96 ng/mL at 1 hour after dosing corresponded with 1610 ng/mL in the dam at 0.5 hours after dosing).

In the fertility and reproduction study in rats, plasma levels of formoterol were measured in pups on post-natal day 15 [see Use in Specific Populations (8.1)]. It was estimated that the maximum plasma concentration that the pups received from the maternal animal, at the highest dose of 15 mg/kg, after nursing was 4.4% (0.24 nmol/L for a litter vs. 5.5 nmol/L for the mother).

8.4 Pediatric Use

BEVESPI AEROSPHERE is not indicated for use in children. The safety and effectiveness of BEVESPI AEROSPHERE in the pediatric population have not been established.

8.5 Geriatric Use

Based on available data, no adjustment of the dosage of BEVESPI AEROSPHERE in geriatric patients is necessary, but greater sensitivity in some older individuals cannot be ruled out.

The confirmatory trials of BEVESPI AEROSPHERE for COPD included 1,680 subjects aged 65 and older and, of those, 290 subjects were aged 75 and older. No overall differences in safety or effectiveness were observed between these subjects and younger subjects.

8.6 Hepatic Impairment

Formal pharmacokinetic studies using BEVESPI AEROSPHERE have not been conducted in patients with hepatic impairment. However, since formoterol fumarate is predominantly cleared by hepatic metabolism, impairment of liver function may lead to accumulation of formoterol fumarate in plasma. Therefore, patients with hepatic disease should be closely monitored.

8.7 Renal Impairment

Formal pharmacokinetic studies using BEVESPI AEROSPHERE have not been conducted in patients with renal impairment. In patients with severe renal impairment (creatinine clearance of ≤30 mL/min/1.73 m^2) or end-stage renal disease requiring dialysis, use of BEVESPI AEROSPHERE should be considered only if the expected benefit outweighs the potential risk [see Clinical Pharmacology (12.3)].

10 OVERDOSAGE

No cases of overdose have been reported with BEVESPI AEROSPHERE. BEVESPI AEROSPHERE contains both glycopyrrolate and formoterol fumarate; therefore, the risks associated with overdosage for the individual components described below apply to BEVESPI AEROSPHERE. Treatment of overdosage consists of discontinuation of BEVESPI AEROSPHERE together with institution of appropriate symptomatic and/or supportive therapy. The judicious use of a cardioselective beta-receptor blocker may be considered, bearing in mind that such medication can produce bronchospasm. Cardiac monitoring is recommended in case of overdosage.

Glycopyrrolate

High doses of glycopyrrolate, a component of BEVESPI AEROSPHERE, may lead to anticholinergic signs and symptoms such as nausea, vomiting, dizziness, lightheadedness, blurred vision, increased intraocular pressure (causing pain, vision disturbances or reddening of the eye), obstipation or difficulties in voiding.

Formoterol Fumarate

An overdose of formoterol fumarate would likely lead to an exaggeration of effects that are typical for beta2-agonists: seizures, angina, hypertension, hypotension, tachycardia, atrial and ventricular tachyarrhythmias, nervousness, headache, tremor, palpitations, muscle cramps, nausea, dizziness, sleep disturbances, metabolic acidosis, hyperglycemia, hypokalemia. As with all sympathomimetic medications, cardiac arrest and even death may be associated with overdosage of formoterol fumarate.

11 DESCRIPTION

BEVESPI AEROSPHERE (glycopyrrolate and formoterol fumarate) Inhalation Aerosol is a pressurized metered-dose inhaler that contains a combination of micronized glycopyrrolate, an anticholinergic, and micronized formoterol fumarate, a long-acting beta2-adrenergic agonist, for oral inhalation.

Glycopyrrolate is a quaternary ammonium salt with the following chemical name: (RS)-[3-(SR)-Hydroxy-1,1-dimethylpyrrolidinium bromide] α-cyclopentylmandelate. Glycopyrrolate is a powder that is freely soluble in water. The molecular formula is C19H28BrNO3, and the molecular weight is 398.33 g/mol. The structural formula is as follows:

Glycopyrrolate contains two chiral centers (denoted by * in structure above) and is a racemate of a 1:1 mixture of the R,S and S,R diastereomers. The active moiety, glycopyrronium, is the positively charged ion of glycopyrrolate.

Formoterol fumarate has the chemical name N-[2-Hydroxy-5-[(1RS)-1-hydroxy-2-[[(1RS)-2-(4-methoxyphenyl)-1- methylethyl]-amino] ethyl]phenyl] formamide, €-2-butenedioate dihydrate. Formoterol fumarate is a powder that is slightly soluble in water. The molecular formula is (C19H24N2O4)2.C4H4O4.2H2O and the molecular weight is 840.91 g/mol. The structural formula is as follows:

Formoterol fumarate contains two chiral centers (denoted by * in structure above), and consists of a single enantiomeric pair (a racemate of R,R and S,S).

BEVESPI AEROSPHERE is formulated as a hydrofluoroalkane (HFA 134a) propelled pressurized metered dose inhaler containing 120 inhalations. The canister has an attached dose indicator and is supplied with a white plastic actuator body and mouthpiece with an orange dust cap.

After priming each actuation of the inhaler meters 10.4 mcg of glycopyrrolate (equivalent to 8.3 mcg of glycopyrronium) and 5.5 mcg of formoterol fumarate from the valve which delivers 9 mcg of glycopyrrolate (equivalent to 7.2 mcg of glycopyrronium) and 4.8 mcg of formoterol fumarate from the actuator. The actual amount of drug delivered to the lung may depend on patient factors, such as the coordination between actuation of the device and inspiration through the delivery system. BEVESPI AEROSPHERE also contains porous particles that form a cosuspension with the drug crystals. The porous particles are comprised of the phospholipid, 1,2-Distearoyl-sn-glycero-3-phosphocholine (DSPC), and calcium chloride. Porous particles and HFA 134a are excipients in the formulation.

12 CLINICAL PHARMACOLOGY

12.1 Mechanism of Action

BEVESPI AEROSPHERE

BEVESPI AEROSPHERE contains both glycopyrrolate and formoterol fumarate. The mechanism of action described below for the individual components applies to BEVESPI AEROSPHERE. These drugs represent two different classes of medications (an anticholinergic, and a long-acting selective beta2-adrenoceptor agonist) that have different effects on clinical physiology and inflammatory indices of COPD.

Glycopyrrolate

Glycopyrrolate is a long-acting antimuscarinic agent which is often referred to as an anticholinergic. It has similar affinity to the subtypes of muscarinic receptors M1 to M5. In the airways, it exhibits pharmacological effects through inhibition of the M3 receptor at the smooth muscle leading to bronchodilation. The competitive and reversible nature of antagonism was shown with human and animal origin receptors and isolated organ preparations. In preclinical in vitro as well as in vivo studies, prevention of methylcholine and acetylcholine-induced bronchoconstrictive effects was dose-dependent and lasted more than 12 hours. The clinical relevance of these findings is unknown. The bronchodilation following inhalation of glycopyrrolate is predominantly a site-specific effect.

Formoterol Fumarate

Formoterol fumarate is a long-acting selective beta2-adrenergic agonist (beta2-agonist) with a rapid onset of action. Inhaled formoterol fumarate acts locally in the lung as a bronchodilator. In vitro studies have shown that formoterol has more than 200-fold greater agonist activity at beta2-receptors than at beta1-receptors. The in vitro binding selectivity to beta2- over beta1-adrenoceptors is higher for formoterol than for albuterol (5 times), whereas salmeterol has a higher (3 times) beta2-selectivity ratio than formoterol.

Although beta2-receptors are the predominant adrenergic receptors in bronchial smooth muscle and beta1-receptors are the predominant receptors in the heart, there are also beta2-receptors in the human heart comprising 10% to 50% of the total beta-adrenergic receptors. The precise function of these receptors has not been established, but they raise the possibility that even highly selective beta2-agonists may have cardiac effects.

The pharmacologic effects of beta2-adrenoceptor agonist drugs, including formoterol fumarate, are at least in part attributable to stimulation of intracellular adenyl cyclase, the enzyme that catalyzes the conversion of adenosine triphosphate (ATP) to cyclic-3', 5'-adenosine monophosphate (cyclic AMP). Increased cyclic AMP levels cause relaxation of bronchial smooth muscle and inhibition of release of mediators of immediate hypersensitivity from cells, especially from mast cells.

12.2 Pharmacodynamics

Cardiac Electrophysiology

The potential for QTc interval prolongation was assessed in a double-blind, single-dose, placebo- and positive-controlled crossover trial in 69 healthy subjects. The largest mean (90% upper confidence bound) differences from placebo in baseline-corrected QTcI for 2 inhalations of BEVESPI AEROSPHERE and glycopyrrolate/formoterol fumarate 72/19.2 mcg, were 3.1 (4.7) ms and 7.6 (9.2) ms, respectively, and excluded the clinically relevant threshold of 10 ms.

A dose-dependent increase in heart rate was also observed. The largest mean (90% upper confidence bound) differences from placebo in baseline-corrected heart rate were 3.3 (4.9) beats/min and 7.6 (9.5) beats/min seen within 10 minutes of dosing with 2 inhalations of BEVESPI AEROSPHERE and glycopyrrolate/formoterol fumarate 72/19.2 mcg, respectively.

Chronic Obstructive Pulmonary Disease

The effect of glycopyrrolate/formoterol fumarate on cardiac rhythm in subjects with COPD was assessed using 24-hour Holter monitoring in 2-week and 24-week trials. All treatments were administered as two inhalations twice daily. In the 2-week trial, the Holter monitoring population included 58 subjects on glycopyrrolate/formoterol fumarate 18/4.8 mcg, 58 subjects on glycopyrrolate 18 mcg, and 60 subjects on formoterol fumarate 4.8 mcg. In the 24-week trial, the Holter monitoring population included 171 subjects on BEVESPI AEROSPHERE, 160 subjects on glycopyrrolate 9 mcg, 174 subjects on formoterol fumarate 4.8 mcg, and 80 subjects on placebo. No clinically meaningful effects on cardiac rhythm were observed.

12.3 Pharmacokinetics

Linear pharmacokinetics were observed for glycopyrrolate (dose range: 18 to 144 mcg) and formoterol fumarate (dose range: 2.4 to 19.2 mcg) after oral inhalation.

Absorption

Glycopyrrolate: Following inhaled administration of BEVESPI AEROSPHERE in subjects with COPD, Cmax occurred at 5 minutes. Steady state is expected to be achieved within 2-3 days of repeated dosing of BEVESPI AEROSPHERE and the extent of exposure is approximately 2.3 times higher than after the first dose.

Formoterol Fumarate: Following inhaled administration of BEVESPI AEROSPHERE in subjects with COPD, Cmax occurred within 20 to 60 minutes. Steady state is expected to be achieved within 2-3 days of repeated dosing with BEVESPI AEROSPHERE and the extent of exposure is approximately 1.5 times higher than after the first dose.

Distribution

Glycopyrrolate: Population pharmacokinetic analysis showed that estimated Vc/F (volume of the central compartment), and V2/F (volume of the peripheral compartment) are 951 L, and 2019 L, respectively.

Formoterol Fumarate: Population pharmacokinetic analysis showed that estimated Vc/F (volume of the central compartment), and V2/F (volume of the peripheral compartment) are 948 L, and 434 L, respectively. Over the concentration range of 10-500 nmol/L, plasma protein binding of formoterol ranged from 46% to 58%.

Elimination

Glycopyrrolate: After IV administration of a 0.2 mg dose of radiolabeled glycopyrrolate, 85% of the dose recovered was recovered in urine 48 hours post dose and some of radioactivity was also recovered in bile. The terminal elimination half-life derived via population pharmacokinetics analysis was 11.8 hours.

Formoterol Fumarate: The excretion of formoterol was studied in four healthy subjects following simultaneous administration of radiolabeled formoterol via the oral and IV routes. In that study, 62% of the radiolabeled formoterol was excreted in the urine while 24% was eliminated in the feces. The terminal elimination half-life derived via population pharmacokinetics analysis was 11.8 hours.

Metabolism

Glycopyrrolate: Based on literature, and an in-vitro human hepatocyte study, metabolism plays a minor role in the overall elimination of glycopyrronium. CYP2D6 was found to be the predominant enzyme involved in the metabolism of glycopyrronium. In-vitro studies indicate the glycopyrrolate does not inhibit any subtype of cytochrome P450 and that there is no induction of CYP1A2, 2B6, or 3A4 at therapeutically relevant concentrations.

Formoterol Fumarate: The primary metabolism of formoterol is by direct glucuronidation and by O-demethylation followed by conjugation to inactive metabolites. Secondary metabolic pathways include deformylation and sulfate conjugation. CYP2D6 and CYP2C have been identified as being primarily responsible for O-demethylation.

Specific Populations

Population pharmacokinetic analysis showed no evidence of a clinically significant effect of age, sex, race/ethnicity, or body weight on the pharmacokinetics of glycopyrrolate and formoterol.

Patients with Hepatic Impairment: Dedicated studies evaluating effect of hepatic impairment on the pharmacokinetics of glycopyrrolate and formoterol were not conducted.

Patients with Renal Impairment: Dedicated studies evaluating effect of renal impairment on the pharmacokinetics of glycopyrrolate and formoterol were not conducted. When glycopyrrolate was administered IV in uremic patients undergoing renal transplantation, mean elimination half-life was significantly longer (46.8 minutes) than in healthy patients (18.6 minutes). The mean AUC (10.6 hr-mcg/L), mean plasma clearance (0.43 L/hr/kg), and mean 3-hour urine excretion (0.7%) for glycopyrrolate were also significantly different than those of controls (3.73 hr-mcg/L, 1.14 L/hr/kg, and 50%, respectively). A population pharmacokinetic analysis using BEVESPI AEROSPHERE showed that formoterol systemic exposure (AUC0-12) in subjects with COPD with moderate renal impairment (45 mL/min creatinine clearance) is expected to be approximately 45% higher compared to subjects with COPD with normal renal function (94 mL/min creatinine clearance).

Drug Interaction Studies

No pharmacokinetic interaction is expected when glycopyrrolate and formoterol fumarate are administered in combination by the inhaled route. Specific drug-drug interaction studies have not been performed with glycopyrrolate or formoterol fumarate.

13 NONCLINICAL TOXICOLOGY

13.1 Carcinogenesis, Mutagenesis, Impairment of Fertility

BEVESPI AEROSPHERE: No studies of carcinogenicity, mutagenicity, or impairment of fertility were conducted with BEVESPI AEROSPHERE; however, separate studies of glycopyrrolate and formoterol fumarate are described below.

Glycopyrrolate

Long-term studies were conducted in mice using inhalation administration and rats using oral administration to evaluate the carcinogenic potential of glycopyrrolate.

In a 24-month inhalation carcinogenicity study in B6C3F1 mice, glycopyrrolate produced no evidence of tumorigenicity when administered to males or females at doses up to 705 and 335 mcg/kg/day, respectively (approximately 95 and 45 times the MRHDID of glycopyrrolate on a mcg/m^2 basis, respectively).

In a 24-month carcinogenicity study in rats, glycopyrrolate produced no evidence of tumorigenicity when administered to males or females by oral gavage at dosages up to 40,000 mcg/kg/day (approximately 11,000 times the MRHDID of glycopyrrolate on a mcg/m^2 basis).

Glycopyrrolate was not mutagenic or clastogenic in the Ames Salmonella/microsome plate test, in vitro mammalian cell micronucleus assay in TK6 cells or the in vivo micronucleus assay in rats.

Fertility and reproductive performance indices were unaffected in male and female rats that received glycopyrrolate by the subcutaneous route at doses up to 10,000 mcg/kg/day (approximately 2700 times the MRHDID on a mcg/m^2 basis).

Formoterol Fumarate

Long-term studies were conducted in mice using oral administration and rats using inhalation administration to evaluate the carcinogenic potential of formoterol fumarate.

In a 24-month carcinogenicity study in CD-1 mice, formoterol fumarate at oral doses of 100 mcg/kg and above (approximately 25 times the MRHDID on a mcg/m^2 basis) caused a dose-related increase in the incidence of uterine leiomyomas.

In a 24-month carcinogenicity study in Sprague-Dawley rats, an increased incidence of mesovarian leiomyoma and uterine leiomyosarcoma were observed at the inhaled dose of 130 mcg/kg (approximately 65 times the MRHDID on a mcg/m^2 basis). No tumors were seen at 22 mcg/kg (approximately 10 times the MRHDID on a mcg/m^2 basis).

Other beta-agonist drugs have similarly demonstrated increases in leiomyomas of the genital tract in female rodents. The relevance of these findings to human use is unknown.

Formoterol fumarate was not mutagenic or clastogenic in the Ames Salmonella/microsome plate test, mouse lymphoma test, chromosome aberration test in human lymphocytes, and rat micronucleus test.

A reduction in fertility and/or reproductive performance was identified in male rats treated with formoterol at an oral dose of 15,000 mcg/kg, (approximately 1900 times the MRHDID on an AUC basis). No such effect was seen at 3,000 mcg/kg (approximately 1500 times the MRHDID on a mcg/m^2 basis). In a separate study with male rats treated with an oral dose of 15,000 mcg/kg (approximately 8000 times the MRHDID on a mcg/m^2 basis), there were findings of testicular tubular atrophy and spermatic debris in the testes and oligospermia in the epididymides. No effect on fertility was detected in female rats at doses up to 15,000 mcg/kg (approximately 1000 times the MRHDID on an AUC basis).

14 CLINICAL STUDIES

The safety and efficacy of BEVESPI AEROSPHERE was evaluated in a clinical development program that included 8 dose-ranging trials and two placebo-controlled lung function trials of 24-weeks duration that included a 28-week extension study to evaluate safety over 1 year. The efficacy of BEVESPI AEROSPHERE is based on the dose ranging trials in 822 subjects with COPD and the 2 placebo-controlled confirmatory trials in 3,705 subjects with COPD.

14.1 Dose-Ranging Trials

Dose selection for BEVESPI AEROSPHERE for COPD was primarily based on data for the individual components, glycopyrrolate and formoterol fumarate, in COPD patients. Based on the findings from these studies, glycopyrrolate/formoterol fumarate 18/9.6 mcg administered twice-daily was evaluated in the confirmatory COPD trials.

Glycopyrrolate

Dose selection for glycopyrrolate was supported by a 14-day, randomized, double-blind, placebo-controlled, incomplete-block crossover trial evaluating 6 doses of glycopyrrolate (GP MDI 18 to 0.6 mcg) administered twice daily and an open-label active control in 140 subjects with COPD. A dose ordering was observed, with the glycopyrrolate 18 mcg demonstrating larger improvements in FEV1 over 12 hours compared with glycopyrrolate 9, 4.6, 2.4, 1.2, and 0.6 mcg (Figure 1).

Figure 1 - Mean Change from Baseline in FEV1 over Time on Day 14 (MITT Population)

The difference from placebo in change from baseline in trough FEV1 after 14 days for the 18, 9, 4.6, 2.4, 1.2, and 0.6 mcg doses were 97 mL (95% CI: 45, 149), 88 mL (95% CI: 37, 139), 75 mL (95% CI: 24, 125), 84 mL (95% CI: 33, 135), 76 mL (95% CI: 22, 129), and 37 mL (95% CI: -17, 91), respectively. Two additional dose ranging trials (single-dose and 7-day trials) in subjects with COPD demonstrated minimal additional benefit at doses above 18 mcg of glycopyrrolate. The results supported the selection of 18 mcg of glycopyrrolate twice daily in the confirmatory COPD trials.

Evaluations of the appropriate dosing interval for glycopyrrolate were conducted by comparing to open-label ipratropium bromide inhalation aerosol administered four times daily. The results supported the selection of a twice-daily dosing interval for further evaluation in the confirmatory COPD trials.

Formoterol Fumarate

Dose selection for formoterol fumarate was supported by a single-dose, randomized, double-blind, placebo-controlled, crossover trial evaluating 3 doses of formoterol fumarate (FF MDI 9.6, 4.8, and 2.4 mcg), an open-label active control, and placebo in 34 subjects with COPD. A dose ordering was observed with the formoterol fumarate 9.6 mcg dose demonstrating larger improvements in FEV1 over 12 hours compared with the lower doses of 4.8 and 2.4 mcg (Figure 2).

Figure 2 - Mean Change from Baseline in FEV1 over Time on Day 1

The differences in mean change from baseline in normalized FEV1 AUC0-12 for formoterol fumarate 9.6, 4.8, and 2.4 mcg compared to placebo were 176 mL (95% CI: 138, 214), 103 (95% CI: 66, 140), and 81 (95% CI: 45, 118), respectively. These results provided support for the selection of 9.6 mcg of formoterol fumarate twice daily in the confirmatory COPD trials.

14.2 Confirmatory Trials

The clinical development program for BEVESPI AEROSPHERE included two (Trial 1 and Trial 2) 24-week, randomized, double-blind, placebo-controlled, parallel-group trials in subjects with moderate to very severe COPD designed to evaluate the efficacy of BEVESPI AEROSPHERE on lung function. The 24-week trials included 3,699 subjects that had a clinical diagnosis of COPD, were between 40 and 80 years of age, had a history of smoking greater than or equal to 10 pack-years, had a post-albuterol FEV1 less than 80% of predicted normal values, and had a ratio of FEV1/FVC of less than 0.7. The majority of patients were male (56%) and Caucasian (91%) with a mean age of 63 years and an average smoking history of 51 pack-years (54% current smokers). During screening, mean post-bronchodilator percent predicted FEV1 was 51% (range: 19% to 82%) and mean percent reversibility was 20% (range: -32% to 135%).

Trial 1 and Trial 2 evaluated BEVESPI AEROSPHERE (glycopyrrolate/formoterol fumarate) 18 mcg/9.6 mcg, glycopyrrolate 18 mcg, formoterol fumarate 9.6 mcg, and placebo administered twice daily (BID). Trial 1 also included an open-label active control. The primary endpoint was change from baseline in trough FEV1 at Week 24 compared with placebo, glycopyrrolate 18 mcg BID, and formoterol fumarate 9.6 mcg BID. The comparison of BEVESPI AEROSPHERE with glycopyrrolate 18 mcg and formoterol fumarate 9.6 mcg was assessed to evaluate the contribution of the individual components to BEVESPI AEROSPHERE. In both trials, BEVESPI AEROSPHERE demonstrated a larger increase in mean change from baseline in trough FEV1 at Week 24 relative to placebo, glycopyrrolate 18 mcg, and formoterol fumarate 9.6 mcg (Table 2).

Table 2 – Least Square (LS) Mean Change from Baseline in Morning Pre-dose Trough
FEV1 (mL) at Week 24 in Trial 1 and Trial 2 (Intent-to-Treat Population)

 |  | Trough FEV1 (mL) at Week 24
 |  | Difference from
Treatment | N | Placebo [The placebo, glycopyrrolate and formoterol fumarate comparators used the same inhaler and excipients as BEVESPI AEROSPHERE.] LS Mean (95% CI) | Glycopyrrolate 18 mcg BID LS Mean (95% CI) | Formoterol Fumarate 9.6 mcg BID LS Mean (95% CI)
Trial 1
BEVESPI AEROSPHERE | 429 | N=161 150 mL (114, 186) | N=344 59 mL (31, 88) | N=367 64 mL (36, 92)
Trial 2
BEVESPI AEROSPHERE | 433 | N=170 103 mL (67, 140) | N=367 54 mL (25, 83) | N=350 56 mL (27, 85)
N = Number in the intent to treat population

With the limited data available, there were consistent improvements in trough FEV1 with respect to age, sex, degree of airflow limitation, GOLD stage, smoking status, or inhaled corticosteroid use.

In Trials 1 and 2, serial spirometric evaluations were performed throughout the 12-hour dosing interval in a subset of subjects (n=718 and n=585, respectively) at Day 1 and Week 12. Results from Trial 1 are shown in Figure 3. In Trial 2, the results for BEVESPI AEROSPHERE in FEV1 AUC0-12h were similar to those observed in Trial 1.

Figure 3 - Mean Change from Baseline in FEV1 over Time at Day 1 and Week 12 (Trial 1)

Day 1

Week 12

In both trials, peak FEV1 was defined as the maximum FEV1 recorded within 2 hours after the dose of trial medication. The mean peak FEV1 improvement from baseline with BEVESPI AEROSPHERE compared with placebo at Week 24 was 291 mL (95% CI: 252, 331) and 267 mL (95% CI: 226, 308) in Trial 1 and Trial 2, respectively. BEVESPI AEROSPHERE demonstrated an onset of bronchodilatory treatment effect at 5 minutes after the first dose based on a mean increase in FEV1 compared to placebo of 187 mL (95% CI: 168, 205) and 186 mL (95% CI: 164, 207) in Trial 1 and Trial 2, respectively. In both Trial 1 and 2, subjects treated with BEVESPI AEROSPHERE used less daily rescue albuterol compared to subjects treated with placebo.

The St. George’s Respiratory Questionnaire (SGRQ) was assessed in Trials 1 and 2. In Trial 1, the SGRQ responder rate (defined as an improvement in score of 4 or more as threshold) was 37%, 30%, 35%, and 28% for BEVESPI AEROSPHERE, glycopyrrolate, formoterol fumarate, and placebo, respectively, with odds ratios of 1.4 (95% CI: 1.1, 1.8), 1.1 (95% CI: 0.9, 1.5), and 1.5 (95% CI: 1.1, 2.1), for BEVESPI AEROSPHERE vs. glycopyrrolate, BEVESPI AEROSPHERE vs. formoterol fumarate, and BEVESPI AEROSPHERE vs. placebo, respectively. In Trial 2, the trends were similar, with odds ratios of 1.2 (95% CI: 0.9, 1.6), 1.3 (95% CI: 1.0, 1.7), and 1.3 (95% CI: 0.9, 1.8), for BEVESPI AEROSPHERE vs. glycopyrrolate, BEVESPI AEROSPHERE vs. formoterol fumarate, and BEVESPI AEROSPHERE vs. placebo, respectively.

16 HOW SUPPLIED/STORAGE AND HANDLING

BEVESPI AEROSPHERE Inhalation Aerosol:

- 9 mcg glycopyrrolate and 4.8 mcg formoterol fumarate per inhalation
- is supplied as a pressurized aluminum canister with an attached dose indicator, a white plastic actuator and mouthpiece, and an orange dust cap
- each 120 inhalation canister has a net fill weight of 10.7 grams (NDC 0310-4600-12)
- each canister is packaged in a foil pouch with desiccant sachet and is placed into a carton
- each carton contains one canister and a Patient Information leaflet

The BEVESPI AEROSPHERE canister should only be used with the BEVESPI AEROSPHERE actuator, and the BEVESPI AEROSPHERE actuator should not be used with any other inhalation drug product.

The correct amount of medication in each inhalation cannot be assured after the label number of inhalations from the canister have been used, when the dose indicator display window shows zero, even though the canister may not feel completely empty. BEVESPI AEROSPHERE should be discarded when the dose indicator display window shows zero or 3 months after removal from the foil pouch, whichever comes first. Never immerse the canister into water to determine the amount remaining in the canister (“float test”).

Store at controlled room temperature 20° to 25°C (68° to 77°F); excursions permitted to 15° to 30°C (59° to 86°F) [see USP].

For best results, the canister should be at room temperature before use. Shake well before using. Keep out of reach of children.

CONTENTS UNDER PRESSURE

Do not puncture. Do not use or store near heat or open flame. Exposure to temperatures above 49°C (120°F) may cause bursting. Never throw canister into fire or incinerator. Avoid spraying in eyes.

17 PATIENT COUNSELING INFORMATION

Advise the patient to read the FDA-approved patient labeling (Patient Information and Instructions for Use)

Serious Asthma-Related Events: Inform patients that LABAs, such as formoterol fumarate, one of the active ingredients in BEVESPI AEROSPHERE, when used alone (without an inhaled corticosteroid), increase the risk of serious asthma-related events, including asthma-related death. BEVESPI AEROSPHERE is not indicated for the treatment of asthma [see Warnings and Precautions (5.1)].

Not for Acute Symptoms: Inform patients that BEVESPI AEROSPHERE is not meant to relieve acute symptoms of COPD and extra doses should not be used for that purpose. Advise them to treat acute symptoms with a rescue inhaler such as albuterol. Provide patients with such medicine and instruct them in how it should be used [see Warnings and Precautions (5.2)].

Instruct patients to seek medical attention immediately if they experience any of the following:

- Symptoms get worse
- Need for more inhalations than usual of their rescue inhaler

Patients should not stop therapy with BEVESPI AEROSPHERE without physician/provider guidance since symptoms may recur after discontinuation.

Do Not Use Additional Long-Acting Beta2-Agonists: Instruct patients to not use other medicines containing a LABA. Patients should not use more than the recommended dose of BEVESPI AEROSPHERE [see Warnings and Precautions (5.3)].

Instruct patients who have been taking inhaled, short-acting beta2-agonists on a regular basis to discontinue the regular use of these products and use them only for the symptomatic relief of acute symptoms.

Paradoxical Bronchospasm: As with other inhaled medicines, BEVESPI AEROSPHERE can cause paradoxical bronchospasm. If paradoxical bronchospasm occurs, instruct patients to discontinue BEVESPI AEROSPHERE [see Warnings and Precautions (5.4)].

Risks Associated With Beta2-Agonist Therapy: Inform patients of adverse effects associated with beta2-agonists, such as palpitations, chest pain, rapid heart rate, tremor, or nervousness. Instruct patients to consult a physician immediately should any of these signs or symptoms develop [see Warnings and Precautions (5.6)].

Worsening of Narrow Angle Glaucoma: Instruct patients to be alert for signs and symptoms of acute narrow-angle glaucoma (e.g., eye pain or discomfort, blurred vision, visual halos, or colored images in association with red eyes from conjunctival congestion and corneal edema). Instruct patients to consult a physician immediately should any of these signs or symptoms develop [see Warnings and Precautions (5.7)].

Worsening of Urinary Retention: Instruct patients to be alert for signs and symptoms of urinary retention (e.g., difficulty passing urine, painful urination). Instruct patients to consult a physician immediately should any of these signs or symptoms develop [see Warnings and Precautions (5.8)].

Instructions for Administering BEVESPI AEROSPHERE

It is important for patients to understand how to correctly administer BEVESPI AEROSPHERE [see Instructions for Use].

Inform patients to use 2 inhalations of BEVESPI AEROSPHERE orally twice daily (2 inhalations in the morning and 2 inhalations in the evening).

Instruct patients to prime BEVESPI AEROSPHERE before using it for the first time. Instruct patients to prime BEVESPI AEROSPHERE by releasing 4 sprays into the air away from their face, shaking well before each spray. Inform patients that BEVESPI AEROSPHERE must be re-primed when the inhaler has not been used for more than 7 days. Instruct patients to re-prime BEVESPI AEROSPHERE by releasing 2 sprays into the air away from their face, shaking well before each spray.

Inform patients that it is very important to clean BEVESPI AEROSPHERE 1 time each week so that medicine will not build up and block the spray through the mouthpiece [see Instructions for Use]. Instruct patients to clean BEVESPI AEROSPHERE by taking the canister out of the actuator, running warm water through the actuator, and allowing the actuator to air-dry overnight. Instruct patients to insert the canister back into the actuator after it is dry, and to re-prime BEVESPI AEROSPHERE. Instruct patients to re-prime BEVESPI AEROSPHERE by releasing 2 sprays into the air away from their face, shaking well before each spray.

Inform patients that if they miss a dose of BEVESPI AEROSPHERE, they should take their next dose at the usual time. Instruct patients to not use BEVESPI AEROSPHERE more often or more puffs than they have been prescribed.

Instruct patients not to spray BEVESPI AEROSPHERE in their eyes. Inform patients that if they accidentally get BEVESPI AEROSPHERE in their eyes, to rinse their eyes with water, and if redness or irritation persists, to consult their healthcare provider.

Distributed by: AstraZeneca Pharmaceuticals LP, Wilmington, DE 19850

BEVESPI, AEROSPHERE and BEVESPI AEROSPHERE are registered trademarks of the AstraZeneca group of companies.

©AstraZeneca 2019

MEDICATION GUIDE

PATIENT INFORMATION
BEVESPI AEROSPHERE®
(be-VES-pee AIR-oh-sfeer)
(glycopyrrolate and formoterol fumarate)
inhalation aerosol, for oral inhalation use

What is BEVESPI AEROSPHERE?
BEVESPI AEROSPHERE combines an anticholinergic, glycopyrrolate, and a long-acting beta2-adrenergic agonist (LABA) medicine, formoterol fumarate.

- Anticholinergic and LABA medicines help the muscles around the airways in your lungs stay relaxed to prevent symptoms such as wheezing, cough, chest tightness, and shortness of breath. These symptoms can happen when the muscles around the airways tighten. This makes it hard to breathe.
- BEVESPI AEROSPHERE is a prescription medicine used to treat COPD. COPD is a chronic lung disease that includes chronic bronchitis, emphysema, or both.
- BEVESPI AEROSPHERE is used long term as 2 inhalations, 2 times each day in the morning and in the evening, to improve symptoms of COPD for better breathing.
- BEVESPI AEROSPHERE is not for use to treat sudden symptoms of COPD. Always have a rescue inhaler (an inhaled, short-acting bronchodilator) with you to treat sudden symptoms. If you do not have a rescue inhaler, contact your healthcare provider to have one prescribed for you.
- BEVESPI AEROSPHERE is not for the treatment of asthma. It is not known if BEVESPI AEROSPHERE is safe and effective in people with asthma.
- BEVESPI AEROSPHERE should not be used in children. It is not known if BEVESPI AEROSPHERE is safe and effective in children.

Do not use BEVESPI AEROSPHERE if you:

- are allergic to glycopyrrolate, formoterol fumarate, or to any of the ingredients in BEVESPI AEROSPHERE. See the end of this Patient Information leaflet for a complete list of ingredients.
- have asthma.

Before using BEVESPI AEROSPHERE, tell your healthcare provider about all of your medical conditions, including if you:

- have heart problems
- have high blood pressure
- have seizures
- have thyroid problems
- have diabetes
- have liver problems
- have eye problems such as glaucoma. BEVESPI AEROSPHERE may make your glaucoma worse.
- have prostate or bladder problems, or problems passing urine. BEVESPI AEROSPHERE may make these problems worse.
- are allergic to any other medicines or food products
- have any other medical conditions
- are pregnant or plan to become pregnant. It is not known if BEVESPI AEROSPHERE may harm your unborn baby.
- are breastfeeding or plan to breastfeed. It is not known if the medicines, glycopyrrolate and formoterol fumarate, in BEVESPI AEROSPHERE pass into your breast milk and if they can harm your baby.

Tell your healthcare provider about all of the medicines you take, including prescription and over-the-counter medicines, vitamins, and herbal supplements. BEVESPI AEROSPHERE and certain other medicines may interact with each other. This may cause serious side effects.
Especially tell your healthcare provider if you take:

- anticholinergics (including tiotropium, ipratropium, aclidinium, and umeclidinium)
- other LABAs (including salmeterol, arformoterol, vilanterol, olodaterol, and indacaterol)
- atropine

Know the medicines you take. Keep a list of them to show your healthcare provider and pharmacist each time you get a new medicine.

How should I use BEVESPI AEROSPHERE?
Read the step-by-step instructions for using BEVESPI AEROSPHERE at the end of this Patient Information.

- Do not use BEVESPI AEROSPHERE unless your healthcare provider has taught you how to use the inhaler and you understand how to use it correctly.
- Use BEVESPI AEROSPHERE exactly as prescribed. Do not use BEVESPI AEROSPHERE more often than prescribed.
- Use 2 inhalations of BEVESPI AEROSPHERE, 2 times each day (in the morning and in the evening).
- If you miss a dose of BEVESPI AEROSPHERE, take your next dose at the same time you normally do. Do not take more than your prescribed dose of BEVESPI AEROSPHERE.
- If you take too much BEVESPI AEROSPHERE, call your healthcare provider or go to the nearest hospital emergency room right away if you have unusual symptoms, such as worsening shortness of breath, chest pain, increased heart rate, or shakiness.
- Do not spray BEVESPI AEROSPHERE in your eyes. If BEVESPI AEROSPHERE gets in your eyes, rinse them well with water. If redness continues, call your healthcare provider.
- Do not stop using BEVESPI AEROSPHERE unless told to do so by your healthcare provider because your symptoms might come back. Your healthcare provider will change your medicines as needed.
- Do not use other medicines that contain a LABA or an anticholinergic for any reason. Ask your healthcare provider or pharmacist if any of your other medicines are LABA or anticholinergic containing medicines.
- BEVESPI AEROSPHERE does not relieve sudden symptoms of COPD. Always have a rescue inhaler with you to treat sudden symptoms. If you do not have a rescue inhaler, call your healthcare provider to have one prescribed for you.
- Call your healthcare provider or get medical care right away if your breathing problems get worse; you need to use your rescue inhaler more often than usual, or your rescue inhaler does not work as well to relieve your symptoms.

What are the possible side effects with BEVESPI AEROSPHERE?
BEVESPI AEROSPHERE can cause serious side effects, including:

- people with asthma who take LABA medicines, such as formoterol fumarate (one of the medicines in BEVESPI AEROSPHERE), without also using a medicine called an inhaled corticosteroid, have an increased risk of serious problems from asthma, including being hospitalized, needing a tube placed in their airway to help them breathe, or death.
- Call your healthcare provider if breathing problems worsen over time while using BEVESPI AEROSPHERE. You may need a different treatment.
- Get emergency medical care if:
  ∘ your breathing problems worsen quickly
  ∘ you use your rescue inhaler medicine, but it does not relieve your breathing problems
- using too much of a LABA medicine may cause:

  ∘ chest pain
  ∘ fast and irregular heartbeat
  ∘ tremor

∘ increased blood pressure
∘ headache
∘ nervousness

- COPD symptoms can get worse over time. If your COPD symptoms worsen over time, do not increase your dose of BEVESPI AEROSPHERE, instead call your healthcare provider.
- sudden breathing problems immediately after inhaling your medicine. If you have sudden breathing problems immediately after inhaling your medicine, stop using BEVESPI AEROSPHERE and call your healthcare provider right away.
- serious allergic reactions. Call your healthcare provider or get emergency medical care if you get any of the following symptoms of a serious allergic reaction:

  ∘ rash
  ∘ hives

∘ swelling of the face, mouth, and tongue
∘ breathing problems

- effects on your heart:

  ∘ increase blood pressure
  ∘ a fast or irregular heartbeat

∘ chest pain

- effects on your nervous system:

  ∘ tremor

∘ nervousness

- changes in laboratory blood levels, including high levels of blood sugar (hyperglycemia) and low levels of potassium (hypokalemia) which may cause symptoms of muscle spasm, muscle weakness or abnormal heart rhythm.
- new or worsened eye problems including acute narrow-angle glaucoma. Acute narrow-angle glaucoma can cause permanent loss of vision if not treated. Symptoms of acute narrow-angle glaucoma may include:

  ∘ eye pain or discomfort
  ∘ nausea or vomiting
  ∘ blurred vision

∘ seeing halos or bright colors around lights
∘ red eyes

If you have these symptoms, call your healthcare provider right away before taking another dose.
2. urinary retention. People who take BEVESPI AEROSPHERE may develop new or worse urinary retention. Symptoms of urinary retention may include:

  ∘ difficulty urinating
  ∘ painful urination

∘ urinating frequently
∘ urination in a weak stream or drips

If you have these symptoms of urinary retention, stop taking BEVESPI AEROSPHERE and call your healthcare provider right away before taking another dose.

Common side effects of BEVESPI AEROSPHERE include: urinary tract infection and cough.

Tell your healthcare provider about any side effect that bothers you or that does not go away.

These are not all the possible side effects of BEVESPI AEROSPHERE. For more information, ask your healthcare provider or pharmacist.

Call your doctor for medical advice about side effects. You may report side effects to FDA at 1-800-FDA-1088.

You may also report side effects to AstraZeneca at 1-800-236-9933.

How should I store BEVESPI AEROSPHERE?

- Store BEVESPI AEROSPHERE at room temperature between 68ºF to 77ºF (20ºC to 25ºC).
- Do not put a hole in the BEVESPI AEROSPHERE canister.
- Do not use or store BEVESPI AEROSPHERE near heat or a flame. Temperatures above 120ºF (49ºC) may cause the canister to burst.
- Do not throw the BEVESPI AEROSPHERE canister into a fire or an incinerator.
- Throw away BEVESPI AEROSPHERE 3 months after you open the foil pouch or when the dose indicator reaches zero “0”, whichever comes first.
- Keep BEVESPI AEROSPHERE and all medicines out of the reach of children.

General Information about the safe and effective use of BEVESPI AEROSPHERE
Medicines are sometimes prescribed for purposes other than those listed in a Patient Information leaflet. Do not use BEVESPI AEROSPHERE for a condition for which it was not prescribed. Do not give your BEVESPI AEROSPHERE to other people, even if they have the same symptoms that you have. It may harm them.
You can ask your healthcare provider or pharmacist for information about BEVESPI AEROSPHERE that is written for health professionals.

Active ingredients: micronized glycopyrrolate and micronized formoterol fumarate
Inactive ingredients: hydrofluoroalkane (HFA 134a) and porous particles (comprised of DSPC [1,2-Distearoyl-sn-glycero-3-phosphocholine] and calcium chloride)
Distributed by: AstraZeneca Pharmaceuticals LP, Wilmington, DE 19850

© AstraZeneca 2019

For more information, call 1-800-236-9933 or go to www.BEVESPI.com.

This Patient Information has been approved by the U.S. Food and Drug Administration Revised: March 2023

Instructions for Use

BEVESPI AEROSPHERE®

(be-VES-pee AIR-oh-sfeer)

(glycopyrrolate and formoterol fumarate)
Inhalation aerosol, for oral inhalation use

Read this Instructions for Use before you start using BEVESPI AEROSPHERE and each time you get a refill. There may be new information. This information does not take the place of talking to your healthcare provider about your medical condition or treatment.

Important Information:

- For oral inhalation use only.
- Use BEVESPI AEROSPHERE exactly as your healthcare provider tells you to.
- If you have any questions about the use of your inhaler, ask your healthcare provider or pharmacist.

Parts of your BEVESPI AEROSPHERE inhaler (See Figure 1):

- BEVESPI AEROSPHERE comes as a canister that fits into an actuator with a dose indicator.
  ∘ Do not use the BEVESPI AEROSPHERE actuator with a canister of medicine from any other inhaler.
  ∘ Do not use the BEVESPI AEROSPHERE canister with an actuator from any other inhaler.

- BEVESPI AEROSPHERE comes with a dose indicator located on the top of the canister (See Figure 1). The dose indicator display window will show you how many puffs of medicine you have left. A puff of medicine is released each time you press the center of the dose indicator.

Before you use BEVESPI AEROSPHERE for the first time make sure that the pointer on the dose indicator is pointing to the right of the “120” inhalation mark in the dose indicator display window (See Figure 1).

- The pointer will be pointing to 120 after 10 puffs are delivered from BEVESPI AEROSPHERE. This means that there are 120 puffs of medicine left in the canister (See Figure 2a).
- The pointer will be pointing between 100 and 120 after you take 10 more puffs. This means that there are 110 puffs of medicine left in the canister (See Figure 2b).
- The pointer will be pointing to 100 after you take 10 more puffs. This means that there are 100 puffs of medicine left in the canister (See Figure 2c).

- The dose indicator display window will continue to move after every 10 puffs. The number in the dose indicator display window will continue to change after every 20 puffs.

- The color in the dose indicator display window will change to red, as shown in the shaded area, when there are only 20 puffs of medicine left in your inhaler (See Figure 2d).

Preparing your BEVESPI AEROSPHERE inhaler for use:

- BEVESPI AEROSPHERE should be at room temperature before you use it.
- Your BEVESPI AEROSPHERE inhaler comes in a foil pouch that contains a drying packet (desiccant).
  ∘ Take the BEVESPI AEROPSHERE inhaler out of the foil pouch.
  ∘ Throw away the pouch and the drying packet. Do not eat or breathe in the contents of the drying packet.

Priming your BEVESPI AEROSPHERE inhaler:

Before you use BEVESPI AEROSPHERE for the first time, you must prime the inhaler.

- Remove the cap from the mouthpiece (See Figure 3). Check inside the mouthpiece for objects before use.
- Hold the inhaler in the upright position away from your face and shake the inhaler well (See Figure 4).

- Press down firmly on the center of the dose indicator until the canister stops moving in the actuator, to release a puff of medicine from the mouthpiece (See Figure 5). You may hear a soft click from the dose indicator as it counts down during use.

- Repeat the priming steps 3 more times (See Figure 4 and Figure 5). Shake the inhaler well before each priming puff.
- After priming 4 times, the dose indicator should be pointing to the right of “120” and your inhaler is now ready to use.

Using your BEVESPI AEROSPHERE inhaler:

Step 1: Remove the cap from the mouthpiece (See Figure 6).

Step 2: Shake the inhaler well before each use (See Figure 7).

Step 3: Hold the inhaler with the mouthpiece pointing towards you and breathe out as fully as you comfortably can through your mouth (See Figure 8).

Step 4: Close your lips around the mouthpiece and tilt your head back, keeping your tongue below the mouthpiece (See Figure 9).

Step 5: While breathing in deeply and slowly, press down on the center of the dose indicator until the canister stops moving in the actuator and a puff of medicine has been released (See Figure 10). Then stop pressing the dose indicator.

Step 6: When you have finished breathing in, remove the mouthpiece from your mouth. Hold your breath as long as you comfortably can, up to 10 seconds (See Figure 11).

Step 7: Breathe out gently (See Figure 12). Repeat steps 2 through 7 to take your second puff of BEVESPI AEROSPHERE.

Step 8: Replace the cap over the mouthpiece right away after use (See Figure 13).

How to clean your BEVESPI AEROSPHERE inhaler:

Clean the inhaler 1 time each week. It is very important to keep your inhaler clean so that medicine will not build-up and block the spray through the mouthpiece (See Figure 14).

Step 1: Take the canister out of the actuator (See Figure 15). Do not clean the canister or let it get wet.

Step 2: Take the cap off the mouthpiece.

Step 3: Hold the actuator under the faucet and run warm water through it for about 30 seconds. Turn the actuator upside down and rinse the actuator again through the mouthpiece for about 30 seconds (See Figure 16).

Step 4: Shake off as much water from the actuator as you can.

Step 5: Look into the actuator and the mouthpiece to make sure any medicine build-up has been completely washed away. If there is any build-up, repeat Steps 3 through 5 in the section “How to clean your BEVESPI AEROSPHERE inhaler”.

Step 6: Let the actuator air-dry overnight (See Figure 17). Do not put the canister back into the actuator if it is still wet.

Step 7: When the actuator is dry, gently press the canister down in the actuator (See Figure 18). Do not press down too hard on the canister. This could cause a puff of medicine to be released.

Step 8: Re-prime your BEVESPI AEROSPHERE inhaler after each cleaning. To re-prime the inhaler, shake the inhaler well and press down on the center of the dose indicator 2 times to release a total of 2 puffs into the air away from your face. Your inhaler is now ready to use.

If you do not use your BEVESPI AEROSPHERE for more than 7 days, you will need to re-prime it before use.

To re-prime the inhaler, shake the inhaler well and press down on the center of the dose indicator 2 times to release a total of 2 puffs into the air away from your face. Your inhaler is now ready to use.

BEVESPI and BEVESPI AEROSPHERE are registered trademarks of the AstraZeneca group of companies.

Distributed by: AstraZeneca Pharmaceuticals LP, Wilmington, DE 19850

©AstraZeneca 2023

This Instructions for Use has been approved by the U.S. Food and Drug Administration.

Revised: March 2023

PRINCIPAL DISPLAY PANEL – 9 mcg/4.8 mcg per inhalation

NDC 0310-4600-12
BEVESPI

AEROSPHERE®

(glycopyrrolate and formoterol

fumarate) Inhalation Aerosol
9 mcg/4.8 mcg per inhalation

For Oral Inhalation only

RX only

Shake inhaler well before using

Inhalation Aerosol

120 inhalations

AstraZeneca